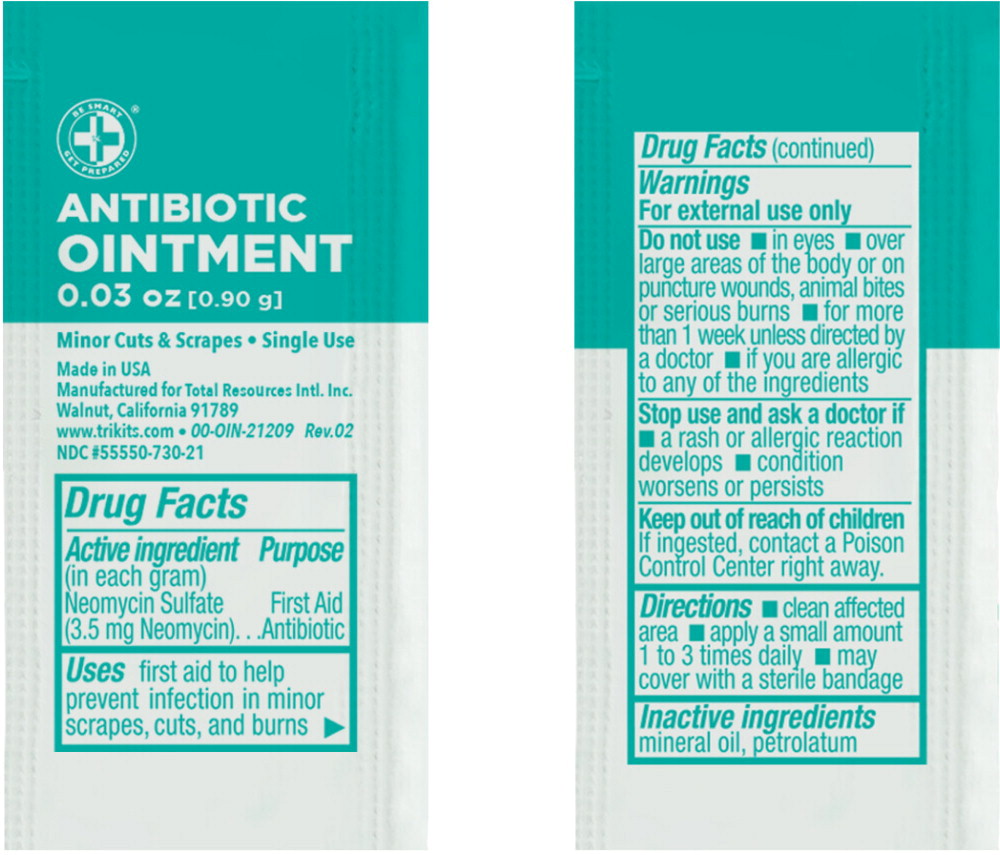 DRUG LABEL: Antibiotic
NDC: 55550-730 | Form: OINTMENT
Manufacturer: Total Resources International
Category: otc | Type: HUMAN OTC DRUG LABEL
Date: 20251010

ACTIVE INGREDIENTS: neomycin sulfate 3.5 mg/1 g
INACTIVE INGREDIENTS: mineral oil; petrolatum

Drug Facts

Active ingredient (in each gram)

Neomycin Sulfate (3.5 mg Neomycin)

Purpose

First Aid Antibiotic

Use

first aid to help prevent infection in minor scrapes, cuts, and burns

Warnings

For external use only

Do not use

- in eyes
- over large areas of the body or on puncture wounds, animal bites or serious burns
- for more than 1 week unless directed by a doctor
- if you are allergic to any of the ingredients

Stop use and ask a doctor if

- a rash or allergic reaction develops
- condition worsens or persists

Keep out of reach of children

If ingested, contact a Poison Control Center right away.

Directions

- clean affected area
- apply a small amount 1 to 3 times daily
- may cover with a sterile bandage

Inactive ingredients

mineral oil, petrolatum

Principal Display Panel – 0.90mL Pouch Label

BE SMART
GET PREPARED®

ANTIBIOTIC OINTMENT

0.03 oz [0.90 g]

Single Use

Made in USA

Manufactured for Total Resources Intl. Inc.

Walnut, California 91789
www.trikits.com • 00-OIN-21209 Rev. 02

NDC 55550-730-21